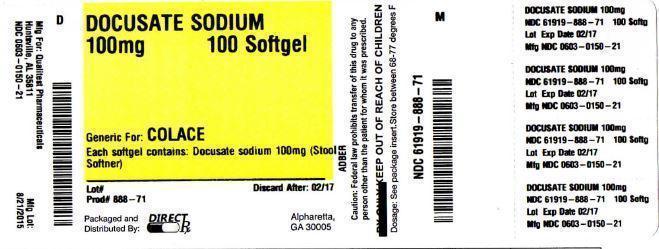 DRUG LABEL: Docusate Sodium
NDC: 61919-888 | Form: TABLET
Manufacturer: Direct Rx
Category: otc | Type: HUMAN OTC DRUG LABEL
Date: 20151104

ACTIVE INGREDIENTS: DOCUSATE SODIUM 100 mg/1 1
INACTIVE INGREDIENTS: FD&C RED NO. 40; FD&C YELLOW NO. 6; GELATIN; GLYCERIN; POLYETHYLENE GLYCOL 400; WATER; SORBITOL

Doc

OTC - ACTIVE INGREDIENT SECTION

Docusate sodium 100 mg

OTC - PURPOSE SECTION

Stool softener

INDICATIONS & USAGE SECTION

relieves occasional constipation (irregularity)
generally produces bowel movement in 12 to 72 hours

OTC - DO NOT USE SECTION

Do not use if you are presently taking mineral oil, unless told to do so by a doctor

OTC - ASK DOCTOR SECTION

stomach pain
nausea
vomiting
noticed a sudden change in bowel habits that lasts over 2 weeks

OTC - STOP USE SECTION

you have rectal bleeding or fail to have a bowel movement after use of a laxative. These could be signs of a serious condition.
you need to use a laxative for more than 1 week

OTC - PREGNANCY OR BREAST FEEDING SECTION

If pregnant or breast-feeding, ask a health professional before use.

OTC - KEEP OUT OF REACH OF CHILDREN SECTION

In case of overdose, get medical help or contact a Poison Control Center right away.

DOSAGE & ADMINISTRATION SECTION

doses may be taken as a single daily dose or in divided doses

OTHER SAFETY INFORMATION

each softgel contains: sodium 5 mg VERY LOW SODIUM
store at 15°-30°C (59°-86°F)
keep tightly closed

You may report serious side effects to: 130 Vintage Drive, Huntsville, AL 35811.

INACTIVE INGREDIENT SECTION

FD&C Red #40, FD&C Yellow #6, gelatin, glycerin, polyethylene glycol 400, purified water, sorbital special

SPL UNCLASSIFIED SECTION

Manufactured for:
QUALITEST PHARMACEUTICALS
HUNTSVILLE, AL 35811

R0 07/2011
015021CPR